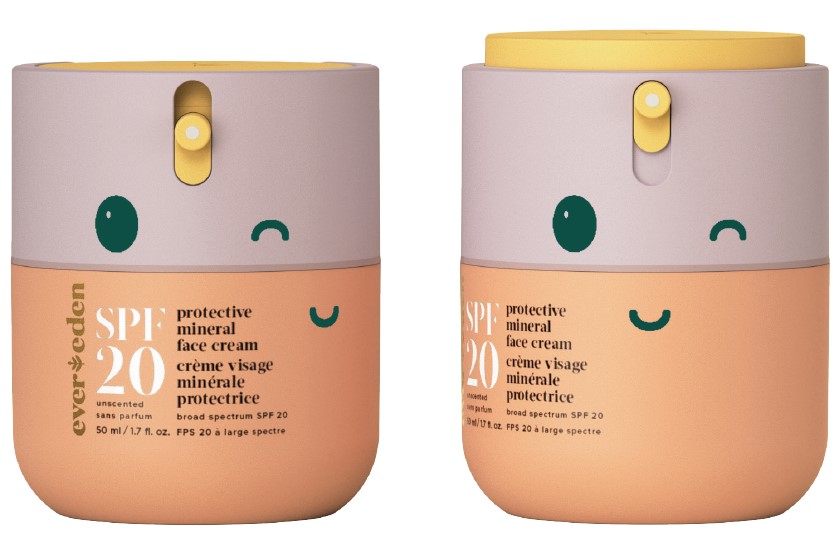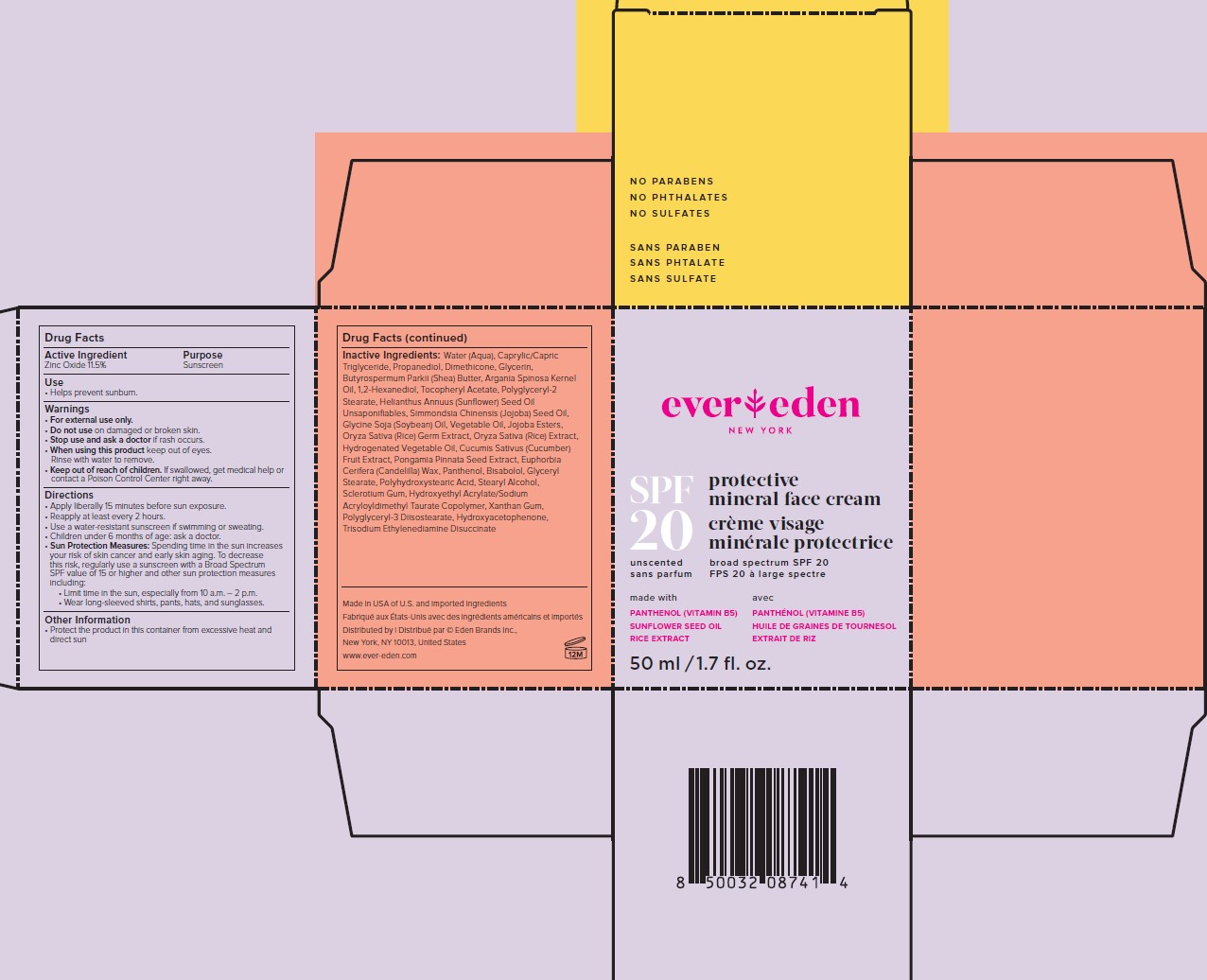 DRUG LABEL: Evereden SPF20 Protective Mineral Face Cream
NDC: 72113-108 | Form: CREAM
Manufacturer: Eden Brands Inc
Category: otc | Type: HUMAN OTC DRUG LABEL
Date: 20241213

ACTIVE INGREDIENTS: ZINC OXIDE 115 mg/1 g
INACTIVE INGREDIENTS: CANDELILLA WAX; POLYHYDROXYSTEARIC ACID (2300 MW); POLYGLYCERIN-3; HYDROXYACETOPHENONE; HYDROXYETHYL ACRYLATE/SODIUM ACRYLOYLDIMETHYL TAURATE COPOLYMER (45000 MPA.S AT 1%); XANTHAN GUM; TRISODIUM ETHYLENEDIAMINE DISUCCINATE; MEDIUM-CHAIN TRIGLYCERIDES; PROPANEDIOL; DIMETHICONE; GLYCERIN; SHEA BUTTER; ARGAN OIL; 1,2-HEXANEDIOL; WATER; ALPHA-TOCOPHEROL ACETATE; POLYGLYCERYL-2 STEARATE; SUNFLOWER OIL UNSAPONIFIABLES; JOJOBA OIL; SOYBEAN OIL; CORN OIL; JOJOBA OIL, RANDOMIZED; RICE GERM; CUCUMBER; PONGAMIA PINNATA SEED; LEVOMENOL; GLYCERYL MONOSTEARATE; STEARYL ALCOHOL; PANTHENOL; BETASIZOFIRAN

SPF20 Protective Mineral Face Cream

ACTIVE INGREDIENT

ACTIVE INGREDIENT: Zinc Oxide, 11.5%

PURPOSE

PURPOSE: Sunscreen

USES:

- Helps prevent sunburn.
- If used as directed with other sun protection measures (see Directions), decreases the risk of skin cancer and early skin aging caused by the sun.

WARNINGS

For external use only.

Do not use on damaged or broken skin.

Stop use and ask a doctor if rash occurs.

When using this product keep out of eyes. Rinse with water to remove.

Keep out of reach of children. If swallowed, get medical help or contact a Poison Control Center right away.

DIRECTIONS

- Apply liberally 15 minutes before sun exposure

- Reapply at least every 2 hours

- Use a water resistant sunscreen if swimming or sweating

- Children under 6 months of age: ask a doctor

- Sun Protection Measures: Spending time in the sun increases your risk of skin cancer and early skin aging. To decrease this risk, regularly use a sunscreen with a Broad Spectrum SPF value of 15 or higher and other sun protection measures including:

-Limit time in the sun, especially from 10am-2pm

-Wear long-sleeved shirts, pants, hats, and sunglasses.

OTHER INFORMATION

Protect the product in this container from excessive heat and direct sun.

INACTIVE INGREDIENTS

Water (Aqua), Caprylic/Capric Triglyceride, Propanediol, Dimethicone, Glycerin, Butyrospermum Parkii (Shea) Butter, Argania Spinosa Kernel Oil, 1,2-Hexanediol, Tocopheryl Acetate, Polyglyceryl-2 Stearate, Helianthus Annuus (Sunflower) Seed Oil Unsaponifiables, Simmondsia Chinensis (Jojoba) Seed Oil, Glycine Soja (Soybean) Oil, Vegetable Oil, Jojoba Esters, Oryza Sativa (Rice) Germ Extract, Oryza Sativa (Rice) Extract, Hydrogenated Vegetable Oil, Cucumis Sativus (Cucumber) Fruit Extract, Pongamia Pinnata Seed Extract, Euphorbia Cerifera (Candelilla) Wax, Panthenol, Bisabolol, Glyceryl Stearate, Polyhydroxystearic Acid, Stearyl Alcohol, Sclerotium Gum, Hydroxyethyl Acrylate/Sodium Acryloyldimethyl Taurate Copolymer, Xanthan Gum, Polyglyceryl-3 Diisostearate, Hydroxyacetophenone, Trisodium Ethylenediamine Disuccinate

RECENT MAJOR CHANGES

Updated DIRECTIONS from Section Type "Indications & Usage" to "Dosage & Administration" on 12/2024. No content changed on the label itself.